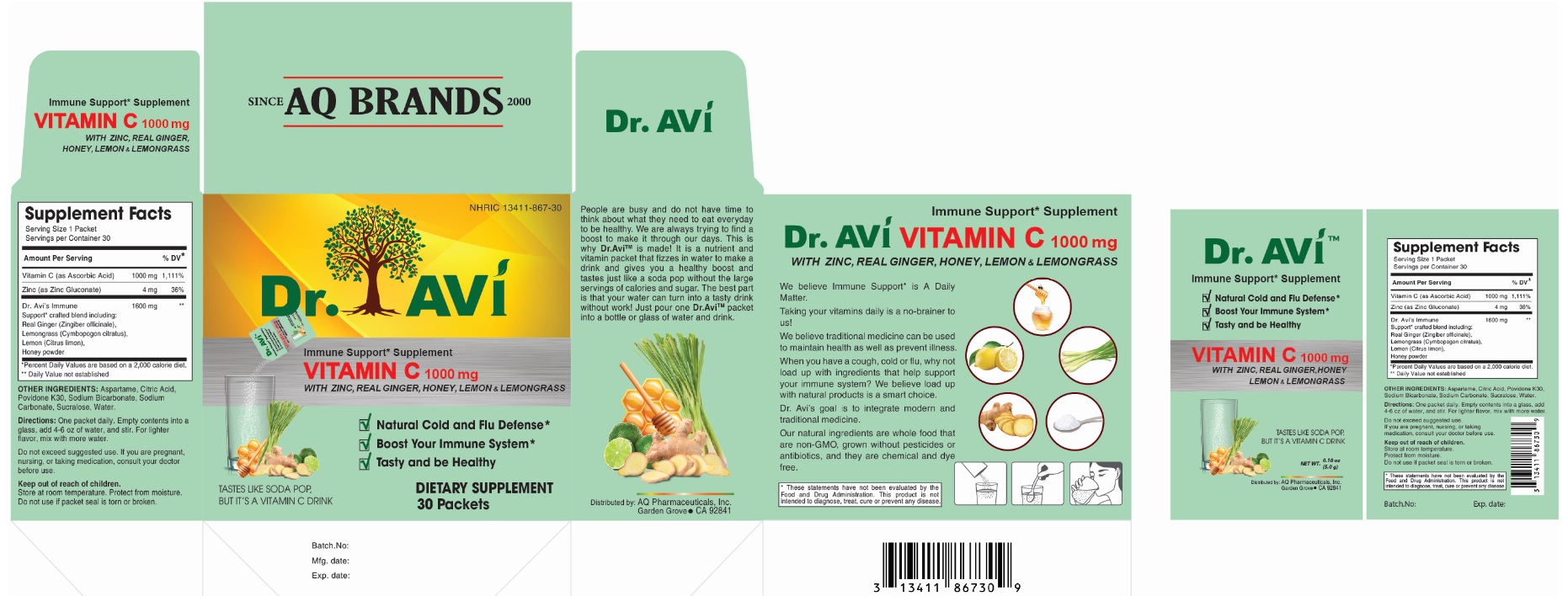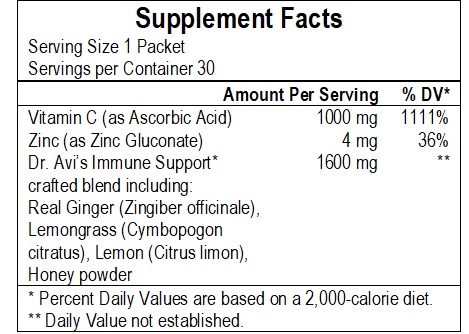 DRUG LABEL: Dr. AVi VITAMIN C 1000 mg with Zinc, Real Ginger, Honey, Lemon and Lemongrass
NDC: 13411-867 | Form: POWDER
Manufacturer: Advanced Pharmaceutical Services, Inc. Dba Affordable Quality Pharmaceuticals
Category: other | Type: DIETARY SUPPLEMENT
Date: 20210308

ACTIVE INGREDIENTS: ASCORBIC ACID 1000 mg/5 g; ZINC GLUCONATE 4 mg/5 g
INACTIVE INGREDIENTS: GINGER; CYMBOPOGON CITRATUS LEAF; CITRUS MEDICA FRUIT; ASPARTAME; CITRIC ACID MONOHYDRATE; POVIDONE K30; SODIUM BICARBONATE; SODIUM CARBONATE; SUCRALOSE; WATER; HONEY

Identity

DIETARY SUPPLEMENT

Warning

Do not exceed suggested use. If you are pregnant, nursing, or taking medication, consult your doctor before use.
KEEP OUT OF REACH OF CHILDREN.

Safe handling and warning

Store at room temperature. Protect from moisture.
Do not use if packet seal is torn or broken.

Health claim

TASTES LIKE SODA POP, BUT IT’S A VITAMIN C DRINK
Immune Support* Supplement VITAMIN C 1000 mg with Zinc, Real Ginger, Honey, Lemon & Lemongrass
- Natural Cold and Flu Defense*
- Boost Your Immune System*
- Tasty and be Healthy
People are busy and do not have time to think about what they need to eat everyday to be healthy. We are always trying to find a boost to make it through our days. This is why Dr. Avi™ is made! It is a nutrient and vitamin packet that fizzes in water to make a drink and gives you a healthy boost and tastes just like a soda pop without the large servings of calories and sugar. The best part is that your water can turn into a tasty drink without work! Just pour one Dr. Avi™ packet into a bottle or glass of water and drink.
We believe Immune Support* Is A Daily Matter.
Taking your vitamins daily is a no-brainer to us!
We believe traditional medicine can be used to maintain health as well as prevent illness.
When you have a cough, cold or flu, why not load up with ingredients that help support your immune system? We believe load up with natural products is a smart choice.
Dr. Avi’s goal is to integrate modern and traditional medicine.
Our natural ingredients are whole food that are non-GMO, grown without pesticides or antibiotics, and they are chemical and dye free

* These statements have not been evaluated by the Food & Drug Administration. This product is not intended to diagnose, treat, cure, or prevent any disease.

Direction

One packet daily. Empty contents into a glass, add 4-6 oz of water, and stir. For lighter flavor, mix with more water.
Do not exceed suggested use. If you are pregnant, nursing, or taking medication, consult your doctor before use.